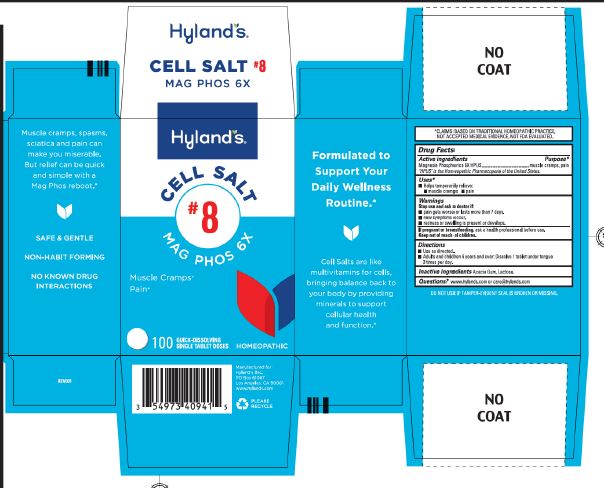 DRUG LABEL: Mag Phos 6X
NDC: 54973-4094 | Form: TABLET, SOLUBLE
Manufacturer: Hyland's Inc.
Category: homeopathic | Type: HUMAN OTC DRUG LABEL
Date: 20241121

ACTIVE INGREDIENTS: MAGNESIUM PHOSPHATE, DIBASIC TRIHYDRATE 6 [hp_X]/1 1
INACTIVE INGREDIENTS: ACACIA; LACTOSE MONOHYDRATE

Cell Salt #8 Mag Phos 6X

Drug Facts

Active ingredients | Purpose
Magnesia Phosphorica 6X HPUS | muscle cramps, pain

"HPUS" is the Homeopathic Pharmacopoeia of the United States.

Uses

■ Temporarily relieves:
■ muscle cramps ■ pain

Warnings

Stop use and ask a doctor if

■ pain gets worse or lasts more than 7 days.
■ new symptoms occur.
■ redness or swelling is present or develops.

If pregnant or breastfeeding

Ask a health professional before use.

Directions

■ Use as directed.
■ Adults and children 6 years and over: Dissolve 1 tablet under tongue 3 times per day.

Inactive ingredients

Acacia Gum, Lactose.

Questions?

www.hylands.com or care@hylands.com

Purpose

Muscle Cramps

Pain

PRINCIPAL DISPLAY PANEL

Hyland's

CELL SALT

#8

Mag Phos 6X

Muscle Cramps*

Pain*

100

QUICK-DISSOLVING

SINGLE TABLET DOSES

HOMEOPATHIC